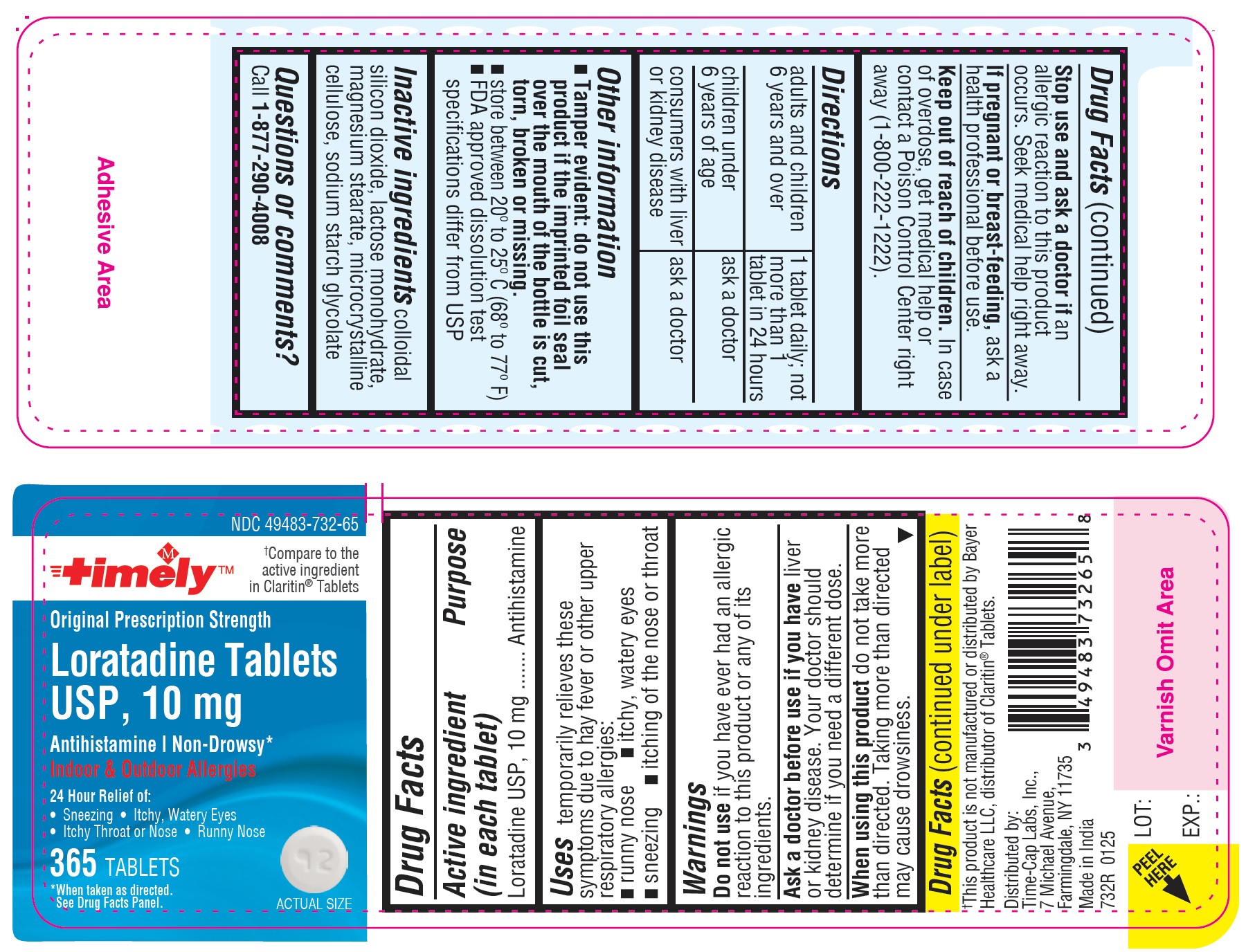 DRUG LABEL: Loratadine 10 mg
NDC: 49483-732 | Form: TABLET
Manufacturer: TIME CAP LABORATORIES, INC.
Category: otc | Type: HUMAN OTC DRUG LABEL
Date: 20250124

ACTIVE INGREDIENTS: LORATADINE 10 mg/1 1
INACTIVE INGREDIENTS: MAGNESIUM STEARATE; SODIUM STARCH GLYCOLATE TYPE A; SILICON DIOXIDE; MICROCRYSTALLINE CELLULOSE 101; LACTOSE MONOHYDRATE

Timely Loratadine Tablets USP, 10 mg

Active ingredient (in each tablet)

Loratadine USP, 10 mg

Purpose

Antihistamine

Uses

temporarily relieves these symptoms due to hay fever or other upper respiratory allergies:

- runny nose
- itchy, watery eyes
- sneezing
- itching of the nose or throat

Warnings

Do not use

if you have ever had an allergic reaction to this product or any of its ingredients.

Ask a doctor before use if you have

liver or kidney disease. Your doctor should determine if you need a different dose.

When using this product

do not take more than directed. Taking more than directed may cause drowsiness

Stop use and ask a doctor if

an allergic reaction to this product occurs. Seek medical help right away.

If pregnant or breast-feeding,

ask a health professional before use.

Keep out of reach of children.

In case of overdose, get medical help or contact a Poison Control Center right away (1-800-222-1222).

Directions

- adults and children 6 years and over: 1 tablet daily; not more than 1 tablet in 24 hours
- children under 6 years of age: ask a doctor
- consumers with liver or kidney disease: ask a doctor

Other information

- Tamper evident: do not use this product if the imprinted foil seal over the mouth of the bottle is cut, torn, broken or missing.
- store between 20º to 25º C (68º to 77º F)
- FDA approved dissolution test specifications differ from USP

Inactive ingredient

colloidal silicon dioxide, lactose monohydrate, magnesium stearate, microcrystalline cellulose, sodium starch glycolate

Questions or comments?

Call 1-877-290-4008